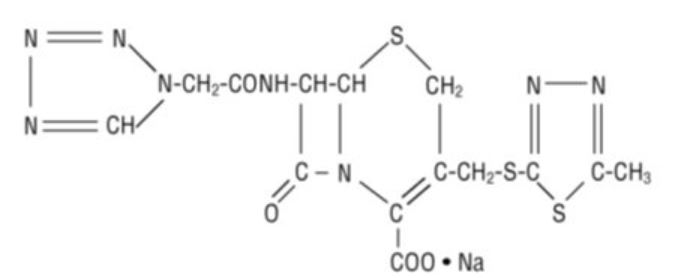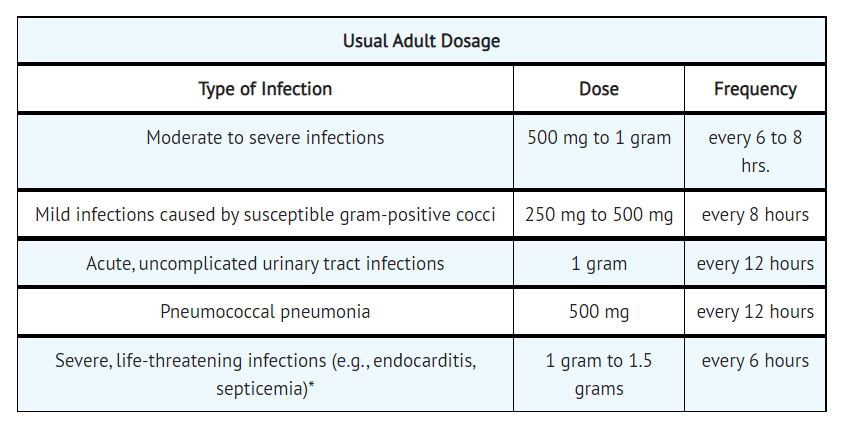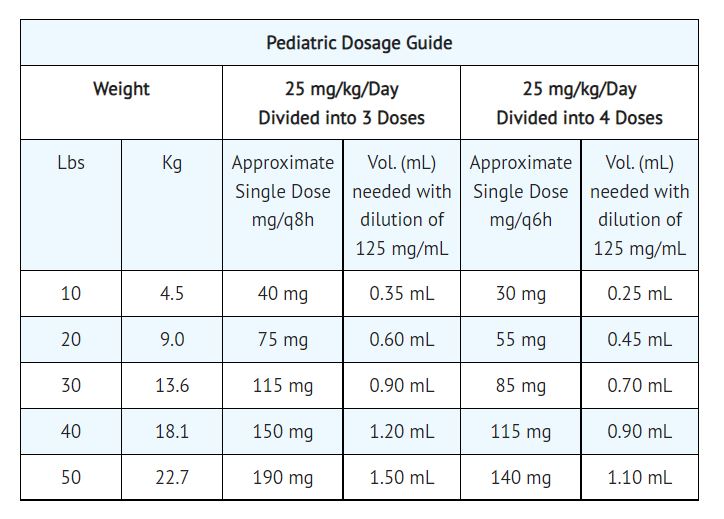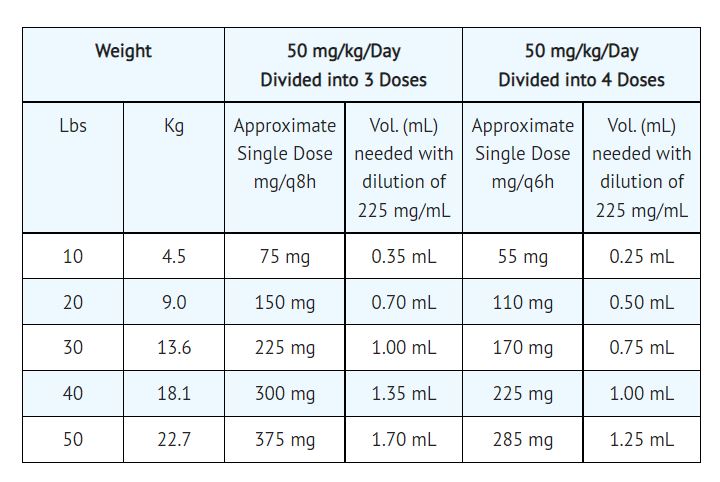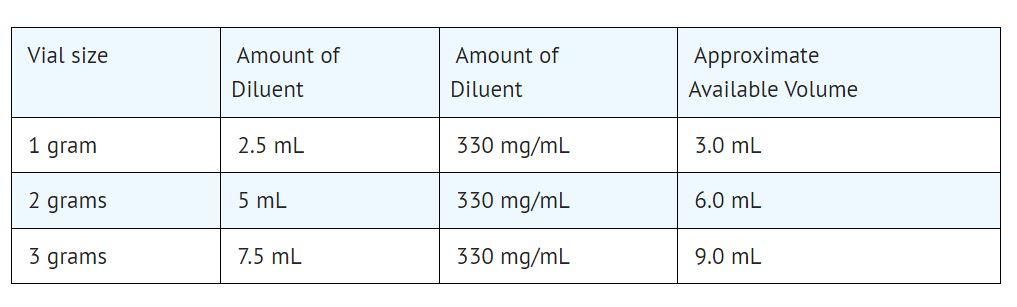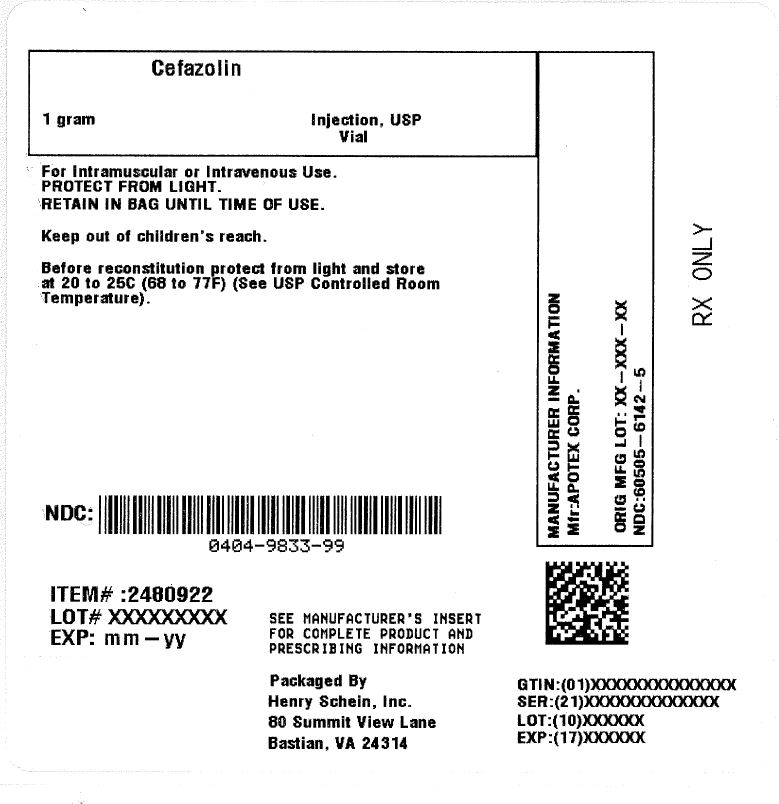 DRUG LABEL: CEFAZOLIN
NDC: 0404-9833 | Form: INJECTION, POWDER, FOR SOLUTION
Manufacturer: Henry Schein, Inc.
Category: prescription | Type: HUMAN PRESCRIPTION DRUG LABEL
Date: 20251027

ACTIVE INGREDIENTS: CEFAZOLIN SODIUM 1 g/1 1

Cefazolin for Injection, USP

TO REDUCE THE DEVELOPMENT OF DRUG-RESISTANT BACTERIA AND MAINTAIN THE EFFECTIVENESS OF CEFAZOLIN FOR INJECTION, USP AND OTHER ANTIBACTERIAL DRUGS, CEFAZOLIN FOR INJECTION, USP SHOULD BE USED ONLY TO TREAT OR PREVENT INFECTIONS THAT ARE PROVEN OR STRONGLY SUSPECTED TO BE CAUSED BY BACTERIA.

Description

Cefazolin for Injection, USP is a semi-synthetic cephalosporin for parenteral administration. It is the sodium salt of 3-{[(5-methyl-1,3,4-thiadiazol-2-yl)thio]-methyl}-8-oxo-7-[2-(1H-tetrazol-1-yl) acetamido]-5-thia-1-azabicyclo [4.2.0]oct-2-ene-2-carboxylic acid.

Structural Formula:

The sodium content is 48 mg (2 mEq sodium ion) per 1 gram of cefazolin.

Cefazolin for Injection, USP is a sterile white or off-white powder or crystalline powder containing Cefazolin Sodium USP supplied in vials equivalent to 1 gram or 2 grams of cefazolin.

Clinical Pharmacology

After intramuscular administration of Cefazolin for Injection, USP to normal volunteers, the mean serum concentrations were 37 mcg/mL at 1 hour and 3 mcg/mL at 8 hours following a 500-mg dose, and 64 mcg/mL at 1 hour and 7 mcg/mL at 8 hours following a 1-gram dose.

Studies have shown that following intravenous administration of Cefazolin for Injection, USP to normal volunteers, mean serum concentrations peaked at approximately 185 mcg/mL and were approximately 4 mcg/mL at 8 hours for a 1-gram dose.

The serum half-life for Cefazolin for Injection, USP is approximately 1.8 hours following IV administration and approximately 2.0 hours following IM administration.

In a study (using normal volunteers) of constant intravenous infusion with dosages of 3.5 mg/kg for 1 hour (approximately 250 mg) and 1.5 mg/kg the next 2 hours (approximately 100 mg), Cefazolin for Injection, USP produced a steady serum level at the third hour of approximately 28 mcg/mL.

Studies in patients hospitalized with infections indicate that Cefazolin for Injection, USP produces mean peak serum levels approximately equivalent to those seen in normal volunteers.

Bile levels in patients without obstructive biliary disease can reach or exceed serum levels by up to 5 times; however, in patients with obstructive biliary disease, bile levels of Cefazolin for Injection, USP are considerably lower than serum levels (< 1.0 mcg/mL).

In synovial fluid, the level of Cefazolin for Injection, USP becomes comparable to that reached in serum at about 4 hours after drug administration.

Studies of cord blood show prompt transfer of Cefazolin for Injection, USP across the placenta. Cefazolin for Injection, USP is present in very low concentrations in the milk of nursing mothers.

Cefazolin for Injection, USP is excreted unchanged in the urine. In the first 6 hours approximately 60% of the drug is excreted in the urine and this increases to 70% to 80% within 24 hours. Cefazolin for Injection, USP achieves peak urine concentrations of approximately 2,400 mcg/mL and 4,000 mcg/mL respectively following 500-mg and 1-gram intramuscular doses.

In patients undergoing peritoneal dialysis (2 L/hr.), Cefazolin for Injection, USP produced mean serum levels of approximately 10 and 30 mcg/mL after 24 hours’ instillation of a dialyzing solution containing 50 mg/L and 150 mg/L, respectively. Mean peak levels were 29 mcg/mL (range 13 to 44 mcg/mL) with 50 mg/L (3 patients), and 72 mcg/mL (range 26 to 142 mcg/mL) with 150 mg/L (6 patients). Intraperitoneal administration of Cefazolin for Injection, USP is usually well tolerated.

Controlled studies on adult normal volunteers, receiving 1 gram 4 times a day for 10 days, monitoring CBC, SGOT, SGPT, bilirubin, alkaline phosphatase, BUN, creatinine, and urinalysis, indicated no clinically significant changes attributed to Cefazolin for Injection, USP.

Microbiology

Mechanism of Action
Cefazolin is a bactericidal agent that acts by inhibition of bacterial cell wall synthesis.

Resistance
Predominant mechanisms of bacterial resistance to cephalosporins include the presence of extended-spectrum beta-lactamases and enzymatic hydrolysis.

Antimicrobial Activity
Cefazolin has been shown to be active against most isolates of the following microorganisms, both in vitro and in clinical infections as described in the INDICATIONS AND USAGE section.

- Gram-Positive Bacteria
- Staphylococcus aureus
- Staphylococcus epidermidis
- Streptococcus agalactiae
- Streptococcus pneumoniae
- Streptococcus pyogenes

Methicillin-resistant staphylococci are uniformly resistant to cefazolin.

- Gram-Negative Bacteria
- Escherichia coli
- Proteus mirabilis

Most isolates of indole positive Proteus (Proteus vulgaris), Enterobacter spp., Morganella morganii, Providencia rettgeri, Serratia spp., and Pseudomonas spp. are resistant to cefazolin.

Susceptibility Testing
For specific information regarding susceptibility test interpretive criteria and associated test methods and quality control standards recognized by FDA for this drug, please see: https://www.fda.gov/STIC.

Indications and Usage

Cefazolin for Injection, USP is indicated in the treatment of the following serious infections due to susceptible organisms:

Respiratory Tract Infections: Due to S. pneumoniae, Klebsiella species, H. influenzae, S. aureus (penicillin-sensitive and penicillin-resistant), and group A beta-hemolytic streptococci.

Injectable benzathine penicillin is considered to be the drug of choice in treatment and prevention of streptococcal infections, including the prophylaxis of rheumatic fever.

Cefazolin for Injection, USP is effective in the eradication of streptococci from the nasopharynx; however, data establishing the efficacy of Cefazolin for Injection, USP in the subsequent prevention of rheumatic fever are not available at present.

Urinary Tract Infections: Due to E. coli, P. mirabilis, Klebsiella species, and some strains of enterobacter and enterococci.

Skin and Skin Structure Infections: Due to S.aureus (penicillin-sensitive and penicillin-resistant), group A beta-hemolytic streptococci, and other strains of streptococci.

Biliary Tract Infections: Due to E. coli, various strains of streptococci, P. mirabilis, Klebsiella species, and S. aureus.

Bone and Joint Infections: Due to S. aureus.

Genital Infections: (i.e., prostatitis, epididymitis) due to E. coli, P. mirabilis, Klebsiella species, and some strains of enterococci.

Septicemia: Due to S. pneumoniae, S. aureus (penicillin-sensitive and penicillin-resistant), P. mirabilis, E. coli, and Klebsiella species.

Endocarditis: Due to S. aureus (penicillin-sensitive and penicillin-resistant) and group A beta-hemolytic streptococci.

Perioperative Prophylaxis: The prophylactic administration of Cefazolin for Injection, USP preoperatively, intraoperatively, and postoperatively may reduce the incidence of certain postoperative infections in patients undergoing surgical procedures which are classified as contaminated or potentially contaminated (e.g., vaginal hysterectomy, and cholecystectomy in high-risk patients such as those older than 70 years, with acute cholecystitis, obstructive jaundice, or common duct bile stones).

The perioperative use of Cefazolin for Injection, USP may also be effective in surgical patients in whom infection at the operative site would present a serious risk (e.g., during open-heart surgery and prosthetic arthroplasty).

The prophylactic administration of Cefazolin for Injection, USP should usually be discontinued within a 24-hour period after the surgical procedure. In surgery where the occurrence of infection may be particularly devastating (e.g., open-heart surgery and prosthetic arthroplasty), the prophylactic administration of Cefazolin for Injection, USP may be continued for 3 to 5 days following the completion of surgery.

If there are signs of infection, specimens for cultures should be obtained for the identification of the causative organism so that appropriate therapy may be instituted. (See DOSAGE AND ADMINISTRATION.)

To reduce the development of drug-resistant bacteria and maintain the effectiveness of Cefazolin for Injection, USP and other antibacterial drugs, Cefazolin for Injection, USP should be used only to treat or prevent infections that are proven or strongly suspected to be caused by susceptible bacteria. When culture and susceptibility information are available, they should be considered in selecting or modifying antibacterial therapy. In the absence of such data, local epidemiology and susceptibility patterns may contribute to the empiric selection of therapy.

Contraindications

CEFAZOLIN FOR INJECTION, USP IS CONTRAINDICATED IN PATIENTS WITH KNOWN ALLERGY TO THE CEPHALOSPORIN GROUP OF ANTIBIOTICS.

Warnings

BEFORE THERAPY WITH CEFAZOLIN FOR INJECTION, USP IS INSTITUTED, CAREFUL INQUIRY SHOULD BE MADE TO DETERMINE WHETHER THE PATIENT HAS HAD PREVIOUS HYPERSENSITIVITY REACTIONS TO CEFAZOLIN, CEPHALOSPORINS, PENICILLINS, OR OTHER DRUGS. IF THIS PRODUCT IS GIVEN TO PENICILLIN-SENSITIVE PATIENTS, CAUTION SHOULD BE EXERCISED BECAUSE CROSS-HYPERSENSITIVITY AMONG BETA-LACTAM ANTIBIOTICS HAS BEEN CLEARLY DOCUMENTED AND MAY OCCUR IN UP TO 10% OF PATIENTS WITH A HISTORY OF PENICILLIN ALLERGY. IF AN ALLERGIC REACTION TO CEFAZOLIN FOR INJECTION, USP OCCURS, DISCONTINUE TREATMENT WITH THE DRUG. SERIOUS ACUTE HYPERSENSITIVITY REACTIONS MAY REQUIRE TREATMENT WITH EPINEPHRINE AND OTHER EMERGENCY MEASURES, INCLUDING OXYGEN, IV FLUIDS, IV ANTIHISTAMINES, CORTICOSTEROIDS, PRESSOR AMINES, AND AIRWAY MANAGEMENT, AS CLINICALLY INDICATED.

Pseudomembranous colitis has been reported with nearly all antibacterial agents, including cefazolin, and may range in severity from mild to life-threatening. Therefore, it is important to consider this diagnosis in patients who present with diarrhea subsequent to the administration of antibacterial agents.

Treatment with antibacterial agents alters the normal flora of the colon and may permit overgrowth of clostridia. Studies indicate that a toxin produced by Clostridium difficile is a primary cause of "antibiotic-associated colitis."

After the diagnosis of pseudomembranous colitis has been established, therapeutic measures should be initiated. Mild cases of pseudomembranous colitis usually respond to drug discontinuation alone. In moderate to severe cases, consideration should be given to management with fluids and electrolytes, protein supplementation, and treatment with an oral antibacterial drug clinically effective against C.difficile colitis.

Precautions

General: Prolonged use of Cefazolin for Injection, USP may result in the overgrowth of nonsusceptible organisms. Careful clinical observation of the patient is essential.

When Cefazolin for Injection, USP is administered to patients with low urinary output because of impaired renal function, lower daily dosage is required (see DOSAGE AND ADMINISTRATION).

As with other β-lactam antibiotics, seizures may occur if inappropriately high doses are administered to patients with impaired renal function (see DOSAGE AND ADMINISTRATION).

Cefazolin for Injection, USP, as with all cephalosporins, should be prescribed with caution in individuals with a history of gastrointestinal disease, particularly colitis.

Cephalosporins may be associated with a fall in prothrombin activity. Those at risk include patients with renal or hepatic impairment or poor nutritional state, as well as patients receiving a protracted course of antimicrobial therapy, and patients previously stabilized on anticoagulant therapy. Prothrombin time should be monitored in patients at risk and exogenous vitamin K administered as indicated.

Prescribing Cefazolin for Injection, USP in the absence of a proven or strongly suspected bacterial infection or a prophylactic indication is unlikely to provide benefit to the patient and increases the risk of the development of drug-resistant bacteria.

Drug Interactions: Probenecid may decrease renal tubular secretion of cephalosporins when used concurrently, resulting in increased and more prolonged cephalosporin blood levels.

Drug/Laboratory Test Interactions: A false positive reaction for glucose in the urine may occur with Benedict's solution, Fehling’s solution or with CLINITEST® tablets, but not with enzyme-based tests such as CLINISTIX®.

Positive direct and indirect antiglobulin (Coombs) tests have occurred; these may also occur in neonates whose mothers received cephalosporins before delivery.

Information for Patients: Patients should be counseled that antibacterial drugs including Cefazolin for Injection, USP, should only be used to treat bacterial infections. They do not treat viral infections (e.g., the common cold). When Cefazolin for Injection, USP is prescribed to treat a bacterial infection, patients should be told that although it is common to feel better early in the course of therapy, the medication should be taken exactly as directed. Skipping doses or not completing the full course of therapy may: (1) decrease the effectiveness of the immediate treatment, and (2) increase the likelihood that bacteria will develop resistance and will not be treatable by Cefazolin for Injection, USP or other antibacterial drugs in the future.

Carcinogenesis/Mutagenesis: Mutagenicity studies and long-term studies in animals to determine the carcinogenic potential of Cefazolin for Injection, USP have not been performed.

Pregnancy: Teratogenic Effects: Pregnancy Category B. Reproduction studies have been performed in rats, mice and rabbits at doses up to 25 times the human dose and have revealed no evidence of impaired fertility or harm to the fetus due to Cefazolin for Injection, USP. There are, however, no adequate and well-controlled studies in pregnant women. Because animal reproduction studies are not always predictive of human response, this drug should be used during pregnancy only if clearly needed.

Labor and Delivery: When cefazolin has been administered prior to caesarean section, drug levels in cord blood have been approximately one quarter to one third of maternal drug levels. The drug appears to have no adverse effect on the fetus.

Nursing Mothers: Cefazolin for Injection, USP is present in very low concentrations in the milk of nursing mothers. Caution should be exercised when Cefazolin for Injection, USP is administered to a nursing woman.

Pediatric Use: Safety and effectiveness for use in premature infants and neonates have not been established. See DOSAGE AND ADMINISTRATION for recommended dosage in pediatric patients older than 1 month.

Geriatric Use: Of the 920 subjects who received Cefazolin for Injection, USP in clinical studies, 313 (34%) were 65 years and over, while 138 (15%) were 75 years and over. No overall differences in safety or effectiveness were observed between these subjects and younger subjects. Other reported clinical experience has not identified differences in responses between the elderly and younger patients, but greater sensitivity of some older individuals cannot be ruled out.

This drug is known to be substantially excreted by the kidney, and the risk of toxic reactions to this drug may be greater in patients with impaired renal function. Because elderly patients are more likely to have decreased renal function, care should be taken in dose selection, and it may be useful to monitor renal function (see PRECAUTIONS, GENERAL and DOSAGE ANDADMINISTRATION).

Adverse Reactions

The following reactions have been reported:

Gastrointestinal: Diarrhea, oral candidiasis (oral thrush), vomiting, nausea, stomach cramps, anorexia, and pseudomembranous colitis. Onset of pseudomembranous colitis symptoms may occur during or after antibiotic treatment (see WARNINGS). Nausea and vomiting have been reported rarely.

Allergic: Anaphylaxis, eosinophilia, itching, drug fever, skin rash, Stevens-Johnson syndrome.

Hematologic: Neutropenia, leukopenia, thrombocytopenia, thrombocythemia.

Hepatic: Transient rise in SGOT, SGPT, and alkaline phosphatase levels has been observed. As with other cephalosporins, reports of hepatitis have been received.

Renal: As with other cephalosporins, reports of increased BUN and creatinine levels, as well as renal failure, have been received.

Local Reactions: Rare instances of phlebitis have been reported at site of injection. Pain at the site of injection after intramuscular administration has occurred infrequently. Some induration has occurred.

Other Reactions: Genital and anal pruritus (including vulvar pruritus, genital moniliasis, and vaginitis).

To report SUSPECTED ADVERSE REACTIONS, contact Apotex Corp. at 1-800-706-5575 or FDA at 1-800-FDA-1088 or www.fda.gov/medwatch.

Dosage and Administration

*In rare instances, doses of up to 12 grams of Cefazolin for Injection, USP per day have been used.

Perioperative Prophylactic Use: To prevent postoperative infection in contaminated or potentially contaminated surgery, recommended doses are:

a. 1 gram IV or IM administered ½ hour to 1 hour prior to the start of surgery.

b. For lengthy operative procedures (e.g., 2 hours or more), 500 mg to 1 gram IV or IM during surgery (administration modified depending on the duration of the operative procedure).

c. 500 mg to 1 gram IV or IM every 6 to 8 hours for 24 hours postoperatively.

It is important that (1) the preoperative dose be given just (½ to 1 hour) prior to the start of surgery so that adequate antibiotic levels are present in the serum and tissues at the time of initial surgical incision; and (2) Cefazolin for Injection, USP be administered, if necessary, at appropriate intervals during surgery to provide sufficient levels of the antibiotic at the anticipated moments of greatest exposure to infective organisms.

In surgery where the occurrence of infection may be particularly devastating (e.g., open-heart surgery and prosthetic arthroplasty), the prophylactic administration of Cefazolin for Injection, USP may be continued for 3 to 5 days following the completion of surgery.

Dosage Adjustment for Patients With Reduced Renal Function: Cefazolin for Injection, USP may be used in patients with reduced renal function with the following dosage adjustments: Patients with a creatinine clearance of 55 mL/min. or greater or a serum creatinine of 1.5 mg % or less can be given full doses. Patients with creatinine clearance rates of 35 to 54 mL/min. or serum creatinine of 1.6 to 3.0 mg % can also be given full doses but dosage should be restricted to at least 8 hour intervals. Patients with creatinine clearance rates of 11 to 34 mL/min. or serum creatinine of 3.1 to 4.5 mg % should be given ½ the usual dose every 12 hours. Patients with creatinine clearance rates of 10 mL/min. or less or serum creatinine of 4.6 mg % or greater should be given ½ the usual dose every 18 to 24 hours. All reduced dosage recommendations apply after an initial loading dose appropriate to the severity of the infection. Patients undergoing peritoneal dialysis: See CLINICAL PHARMACOLOGY.

Pediatric Dosage: In pediatric patients, a total daily dosage of 25 to 50 mg per kg (approximately 10 to 20 mg per pound) of body weight, divided into 3 or 4 equal doses, is effective for most mild to moderately severe infections. Total daily dosage may be increased to 100 mg per kg (45 mg per pound) of body weight for severe infections. Since safety for use in premature infants and in neonates has not been established, the use of Cefazolin for Injection, USP in these patients is not recommended.

In pediatric patients with mild to moderate renal impairment (creatinine clearance of 70 to 40 mL/min.), 60 percent of the normal daily dose given in equally divided doses every 12 hours should be sufficient. In patients with moderate impairment (creatinine clearance of 40 to 20 mL/min.), 25 percent of the normal daily dose given in equally divided doses every 12 hours should be adequate. Pediatric patients with severe renal impairment (creatinine clearance of 20 to 5 mL/min.) may be given 10 percent of the normal daily dose every 24 hours. All dosage recommendations apply after an initial loading dose.

RECONSTITUTION
Preparation of Parenteral Solution: Parenteral drug products should be SHAKEN WELL when reconstituted, and inspected visually for particulate matter prior to administration. If particulate matter is evident in reconstituted fluids, the drug solutions should be discarded.

When reconstituted or diluted according to the instructions below, Cefazolin for Injection, USP is stable for 24 hours at room temperature or for 10 days if stored under refrigeration (5°C or 41 °F). Reconstituted solutions may range in color from pale yellow to yellow without a change in potency.

Single-Dose Vials: For IM injection, IV direct (bolus) injection or IV infusion, reconstitute with Sterile Water for Injection according to the following table. SHAKE WELL.

ADMINISTRATION
Intramuscular Administration: Reconstitute vials with Sterile Water for Injection according to the dilution table above. Shake well until dissolved. Cefazolin for Injection, USP should be injected into a large muscle mass. Pain on injection is infrequent with Cefazolin for Injection, USP.

Intravenous Administration: Direct (bolus) injection: Following reconstitution according to the above table, further dilute vials with approximately 5 mL Sterile Water for Injection. Inject the solution slowly over 3 to 5 minutes, directly or through tubing for patients receiving parenteral fluids (see list below).

Intermittent or continuous infusion: Dilute reconstituted Cefazolin for Injection, USP in 50 to 100 mL of 1 of the following solutions:

Sodium Chloride Injection, USP

5% or 10% Dextrose Injection, USP

5% Dextrose in Lactated Ringer's Injection, USP

5% Dextrose and 0.9% Sodium Chloride Injection, USP

5% Dextrose and 0.45% Sodium Chloride Injection, USP

5% Dextrose and 0.2% Sodium Chloride Injection, USP

Lactated Ringer's Injection, USP

Invert Sugar 5% or 10% in Sterile Water for Injection

Ringer's Injection, USP

5% Sodium Bicarbonate Injection, USP

How Supplied

Each vial of Cefazolin for Injection, USP contains cefazolin sodium equivalent to 1 gram 2 grams, or 3 grams cefazolin.

NDC 60505-6142-5, 1 gram, carton of 25 vials

NDC 60505-6231-5, 2 grams, carton of 25 vials

NDC 60505-6266-5, 3 grams, carton of 25 vials

As with other cephalosporins, cefazolin tends to darken depending on storage conditions; within the stated recommendations, however, product potency is not adversely affected.

Before reconstitution protect from light and store at 20° to 25° C (68° to 77°F) [See USP Controlled Room Temperature].

CLINITEST is a registered trademark of Miles, Inc.
CLINISTIX is a registered trademark of Bayer Corporation.

Product repackaged by: Henry Schein, Inc., Bastian, VA 24314
From Original Manufacturer/Distributor's NDC and Unit of Sale | To Henry Schein Repackaged Product NDC and Unit of Sale | Total Strength/Total Volume (Concentration) per unit
NDC 60505-6142-5 Carton of 25 vials | NDC 0404-9833-99 1 vial in a bag (Vial bears NDC 60505-6142-0) | 1 gram

Manufactured by:
Manufactured by:
Qilu Pharmaceutical Co., Ltd.
High Tech Zone
Jinan, 250101, China

Manufactured for:

Apotex Corp.
Weston, Florida, USA 33326

Code number: 34040001011G

Rev 12/22